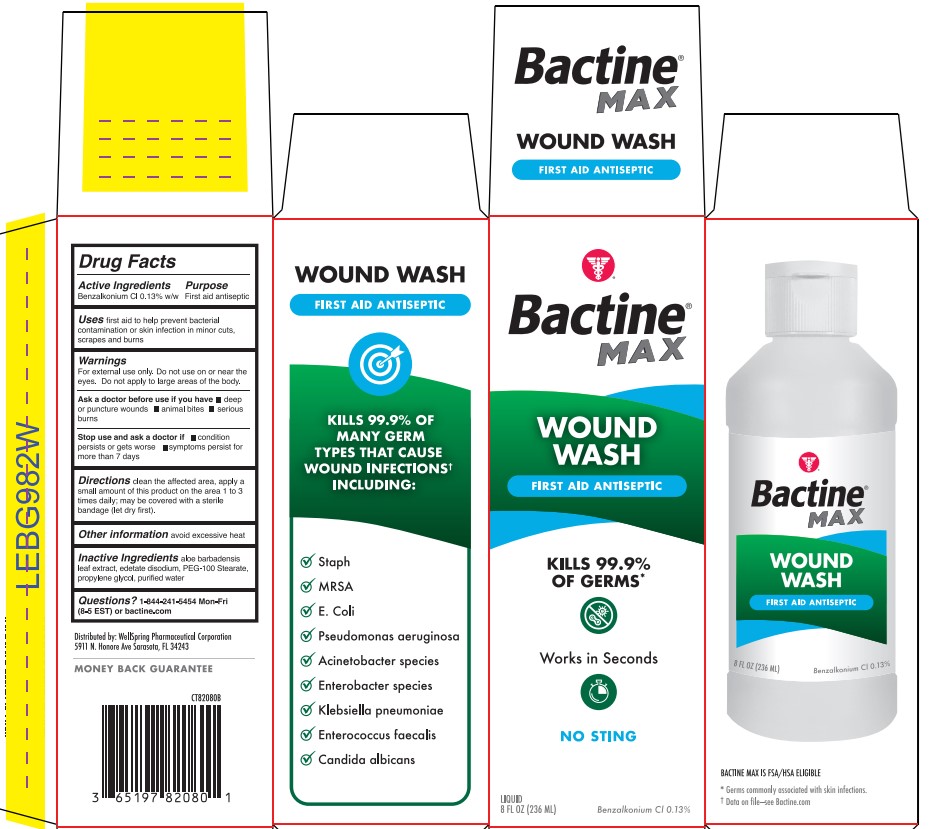 DRUG LABEL: BACTINE
NDC: 65197-820 | Form: LIQUID
Manufacturer: WellSpring Pharmaceutical Corporation
Category: otc | Type: HUMAN OTC DRUG LABEL
Date: 20250108

ACTIVE INGREDIENTS: BENZALKONIUM CHLORIDE 0.13 g/100 mL
INACTIVE INGREDIENTS: EDETATE DISODIUM; PEG-100 STEARATE; PROPYLENE GLYCOL; WATER; ALOE VERA LEAF

BACTINE MAX WOUND WASH

Active ingredient

Benzalkonium Cl 0.13% w/w

Purpose

First aid antiseptic

Use

First aid to help prevent bacterial contamination or skin infection in minor cuts, scrapes and burns.

Warning

For external use only. Do not use on or near the eyes. Do not apply to large areas of the body. Ask a doctor before use if -you have - deep or puncture wounds - animal bites - serious burns. Stop use and ask doctor if - condition persists or get worse - symptoms persist for more than 7 days.

Directions

Clean the affected area, apply a small amount of this product on the area 1 to 3 times daily; may be covered with a sterile bandage (let dry first).

Other information

Avoid excessive heat

Inactive ingredients

aloe barbadensis leaf extract, edetate disodium, PEG-100 Stearate, propylene glycol, purified water

Questions?

1-844-241-5454 Mon-Fri (8-5 EST) or bactine.com

Bactine Wound Wash Label

Bactine Max Wound Wash IFC Label